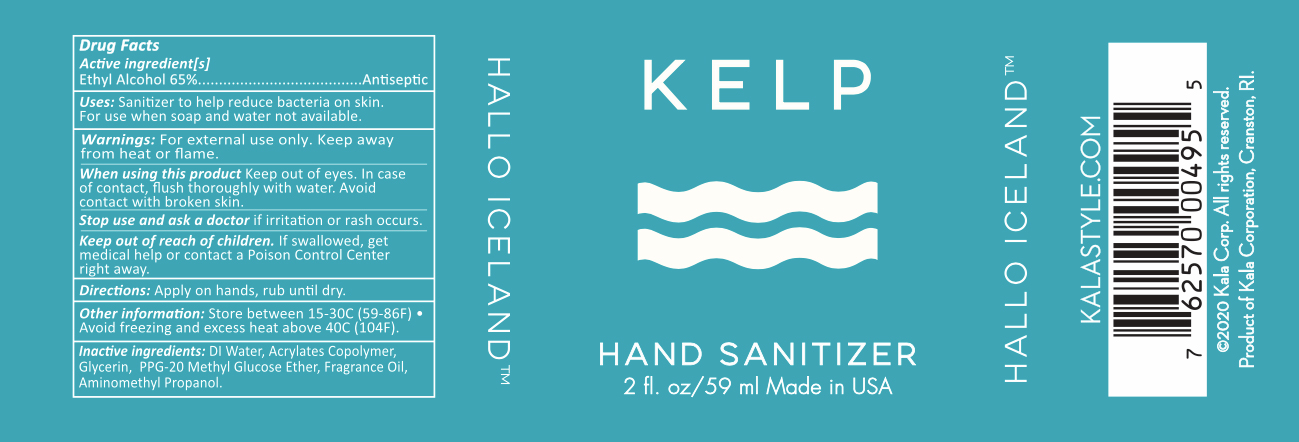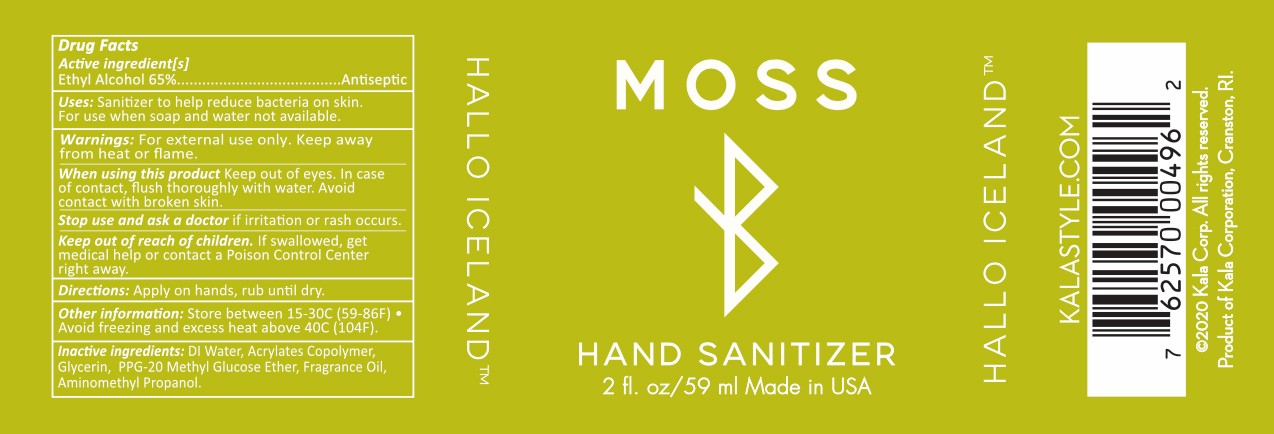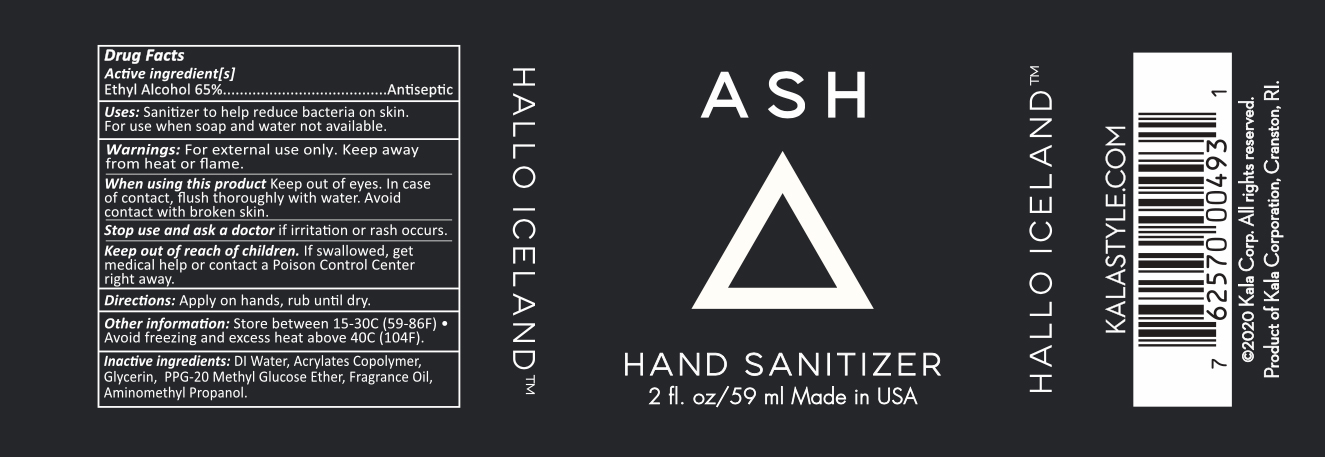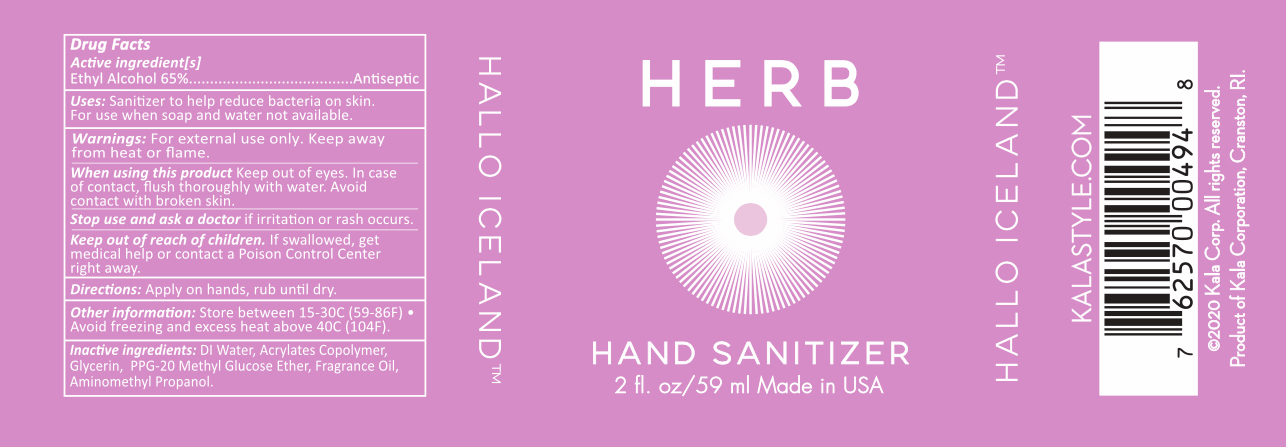 DRUG LABEL: Hallo Sapa Volcanic Ash Hand Sanitizer
NDC: 79655-493 | Form: SPRAY
Manufacturer: Kala Corporation
Category: otc | Type: HUMAN OTC DRUG LABEL
Date: 20220113

ACTIVE INGREDIENTS: ALCOHOL 33 g/55 g
INACTIVE INGREDIENTS: GLYCERIN 0.55 g/55 g; PPG-20 METHYL GLUCOSE ETHER 0.275 g/55 g; ACRYLATES CROSSPOLYMER-6 0.55 g/55 g; WATER 19.8 g/55 g; AMINOMETHYLPROPANOL 0.01 g/55 g

Hallo Iceland Hand Sanitizers

Active Ingredients

Ethyl Alcohol 65% Antiseptic

Uses

Sanitizer to help reduce bacteria on skin. For use when soap and water not available.

Uses

Sanitizer to help reduce bacteria on skin. For use when soap and water not available.

Warnings

For external use only. Keep away from heat or flame.

When using This Product

Keep out of eyes. In case of contact, flush thoroughly with water. Avoid contact with broken skin.

Stop use and ask a doctor

if irritation or rash occurs.

Keep out of reach of children.

If swallowed, get medical help or contact Poison Control center right away.

Directions

Apply on hands, rub until dry.

Other information

Store between 15-30C (58-86F) Avoid freezing and excess heat above 40C (104F)

Inactive ingredients

Deionized Water, Acrylates Copolymer, Glycerin, PPG20 Methyl Glucose Ether, Fragrance Oil, Aminomethyl Propanol.